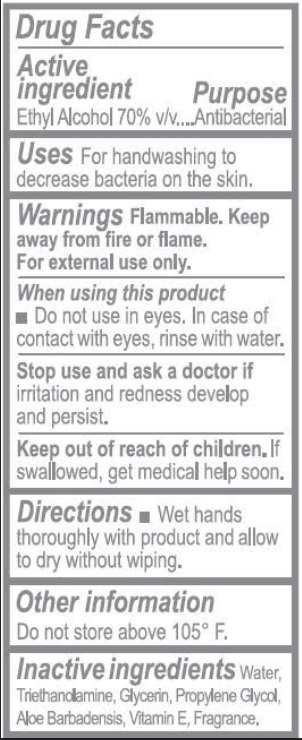 DRUG LABEL: Sani-Pen
NDC: 20590-003 | Form: LIQUID
Manufacturer: Natural Trends, LLC
Category: otc | Type: HUMAN OTC DRUG LABEL
Date: 20200814

ACTIVE INGREDIENTS: ALCOHOL 70 mL/100 mL
INACTIVE INGREDIENTS: ALOE; PROPYLENE GLYCOL; TROLAMINE; .ALPHA.-TOCOPHEROL; GLYCERIN; WATER

Active Ingredient

Ethyl Alcohol 70% v/v.

Purpose

Antibacterial

Uses

For handwashing to decrease bacteria on the skin.

Warnings

Flammable. Keep away from fire or flame

For external use only.

When using this product

Do not use in eyes. In case of contact with eyes, rinse with water.

Stop use & ask a doctor if irritation & redness develop & persist.

Keep out of reach of children. If swallowed, get medical help soon.

Directions

Wet hands thoroughly with product and allow to dry without wiping.

Other information

Do not store above 105° F.

Inactive ingredients

Water, Triethanolamine, Glycerin, Propylene glycol, Aloe Barbadensis, Vitamine E, Fragrance